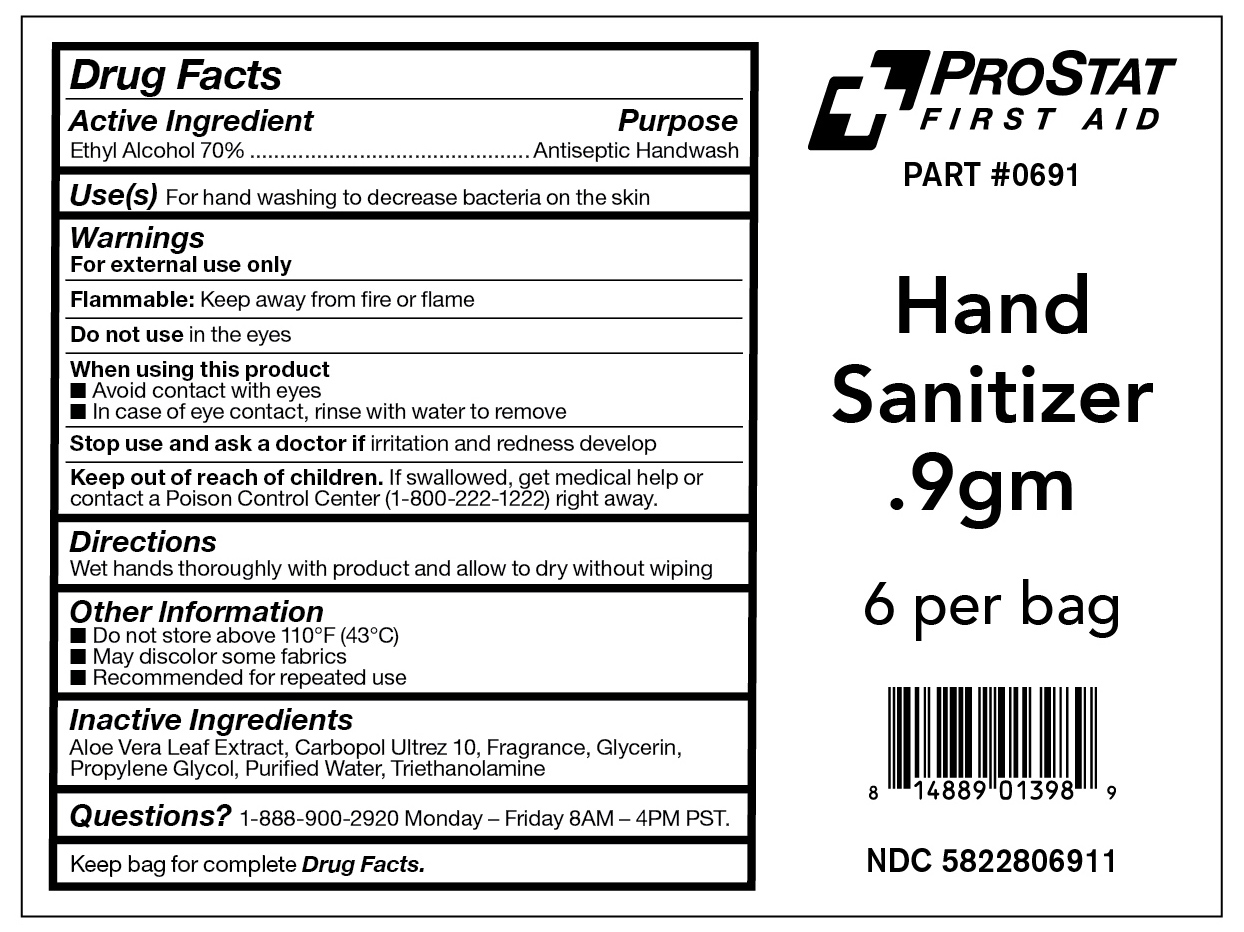 DRUG LABEL: Hand Sanitizer
NDC: 58228-0691 | Form: GEL
Manufacturer: Prostat First Aid LLC
Category: otc | Type: HUMAN OTC DRUG LABEL
Date: 20251215

ACTIVE INGREDIENTS: ALCOHOL 70 mL/100 mL
INACTIVE INGREDIENTS: ALOE VERA LEAF; WATER; PROPYLENE GLYCOL; GLYCERIN; TROLAMINE; CARBOMER INTERPOLYMER TYPE A (ALLYL SUCROSE CROSSLINKED)

PS-0691

Active Ingredient

Ethyl Alcohol 70% v/v

Purpose

Antiseptic Handwash

Use(s)

For hand washing to decrease bacteria on the skin

Warnings

For External Use Only

Flammable. Keep away from fire or flame

Do not use

In the eyes

When using this product

• Avoid contact with eyes

• In case of eye contact, rinse with water to remove

Stop use and ask a doctor if

Irritation and redness develop

Keep out of reach of children

If swallowed, get medical help or contact a Poison Control Center (1-800-222-1222) right away.

Directions

Wet hand thoroughly with product and allow to dry without wiping

Other Information

• Do not store above 110•F (43ºC)

• May discolor some fabrics

• Recommended for repeated use

Inactive Ingredients

Aloe Vera Leaf Extract, Carbopol Ultrez 10, Fragrance, Glycerin, Propylene Glycol, Purified Water, Triethanolamine

Questions?

1-888-900-2920 Monday-Friday 8AM-4PM PST.